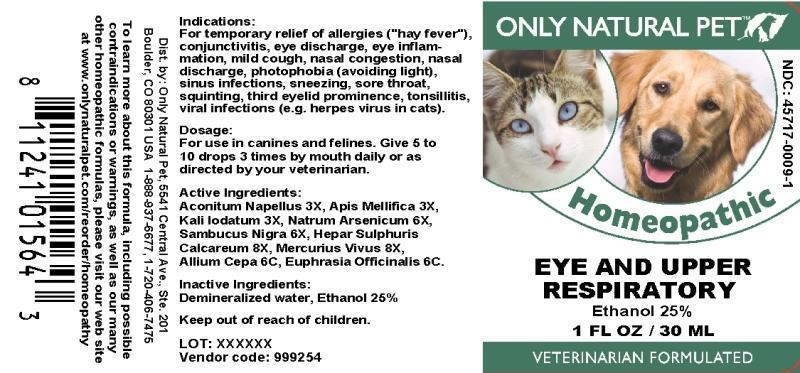 DRUG LABEL: Eye and Upper Respiratory
NDC: 45717-0009 | Form: LIQUID
Manufacturer: Only Natural Pet Store
Category: homeopathic | Type: OTC ANIMAL DRUG LABEL
Date: 20241003

ACTIVE INGREDIENTS: ACONITUM NAPELLUS WHOLE 3 [hp_X]/1 mL; APIS MELLIFERA 3 [hp_X]/1 mL; POTASSIUM IODIDE 3 [hp_X]/1 mL; SODIUM ARSENATE, DIBASIC, HEPTAHYDRATE 6 [hp_X]/1 mL; SAMBUCUS NIGRA FLOWERING TOP 6 [hp_X]/1 mL; CALCIUM SULFIDE 8 [hp_X]/1 mL; MERCURY 8 [hp_X]/1 mL; ONION 6 [hp_C]/1 mL; EUPHRASIA STRICTA 6 [hp_C]/1 mL
INACTIVE INGREDIENTS: WATER; ALCOHOL

DRUG FACTS:

ACTIVE INGREDIENTS:

Aconitum Napellus 3X, Apis Mellifica 3X, Kali Iodatum 3X, Natrum Arsenicum 6X, Sambucus Nigra 6X, Hepar Sulphuris Calcareum 8X, Mercurius Vivus 8X, Allium Cepa 6C, Euphrasia Officinalis 6C

INDICATIONS:

For temporary relief of allergies ("hay fever"), conjunctivitis, eye discharge, eye inflammation, mild cough, nasal congestion, nasal discharge, photophobia (avoiding light), sinus infections, sneezing, sore throat, squinting, third eyelid prominence, tonsillitis, viral infections (e.g. herpes virus in cats).

WARNINGS:

To learn more about this formula, including possible contraindications or warnings, as well as our many other homeopathic formulas, please visit our web site at www.onlynaturalpet.com/reorder/homeopathy

KEEP OUT OF REACH OF CHILDREN:

DIRECTIONS:

For use in canines and felines. Give 5 to 10 drops 3 times by mouth daily or as directed by your veterinarian.

INDICATIONS:

For temporary relief of allergies ("hay fever"), conjunctivitis, eye discharge, eye inflammation, mild cough, nasal congestion, nasal discharge, photophobia (avoiding light), sinus infections, sneezing, sore throat, squinting, third eyelid prominence, tonsillitis, viral infections (e.g. herpes virus in cats).

INACTIVE INGREDIENTS:

Demineralized water, Ethanol 25%

QUESTIONS:

Dist. by: Only Natural Pet, 5541 Central Ave., Ste. 201

Boulder, CO 80301 USA 1-888-937-6677, 1-720-406-7475

PACKAGE LABEL DISPLAY:

ONLY NATURAL PET

NDC : 45717-0009-1

Homeopathic

EYE AND UPPER

RESPIRATORY

1 FL OZ / 30ML